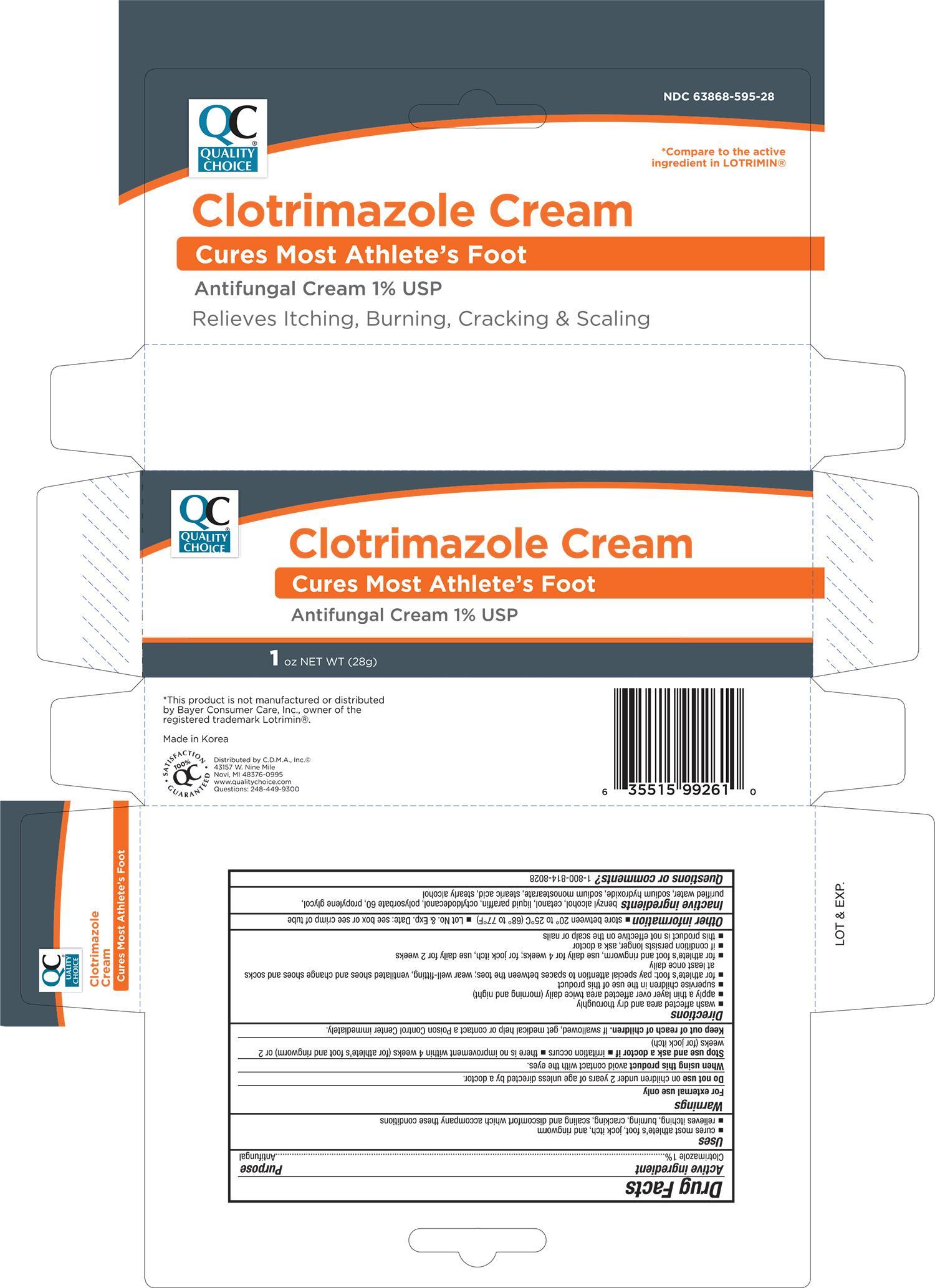 DRUG LABEL: Quality Choice Clotrimazole
NDC: 63868-595 | Form: CREAM
Manufacturer: Chain Drug Marketing Association
Category: otc | Type: HUMAN OTC DRUG LABEL
Date: 20191209

ACTIVE INGREDIENTS: CLOTRIMAZOLE 10 mg/1 g
INACTIVE INGREDIENTS: BENZYL ALCOHOL; PARAFFIN; OCTYLDODECANOL; POLYSORBATE 60; PROPYLENE GLYCOL; WATER; SODIUM HYDROXIDE; STEARIC ACID; STEARYL ALCOHOL

QC Clotrimazole Cream 1 oz 99261, 2019

Active ingredient Purpose

Clotrimazole 1%.................................................................. Antifungal

Uses

- cures most athlete's foot, jock itch, and ringworm

Warnings

For external use only

Do not use on children under 2 years of age unless directed by a doctor

When using this product avoid contact with the eyes

Stop use and ask a doctor if

- irritation occurs
- there is no iprovement within 4 weeks (for athlete's foot and ringworm) or 2 weeks (for jock itch)

Keep out of reach of children. If swallowed, get medical help or contact a Poison Control Center immediately.

Directions

- wash affected area and dry thoroughly
- apply a thin layer over affected area twice daily (morning and night)
- supervise children in the use of this product
- for athlete's foot: pay special attention to spaces between the toesl; wear well-fitting, ventilated shoes and change shoes and socks at least once daily
- if condition persists longer, ask a doctor
- this product is not effective on the scalp or nails

Other information

- store between 20° to 25°C (68° to 77°F)
- Lot No. & Exp. Date: see box or see crimp of tube

INACTIVE INGREDIENT

Inactive ingredients benzyl alcohol, cetanol, liquid paraffin, octyldodecanol, polysorbate 60, propylene glycol, purified water, sodium hydroxide, sodium monostearate, stearic acid, stearyl alcohol

DOSAGE AND ADMINISTRATION

DISTRIBUTED BY C.D.M.A., INC.

43157 W. NINE MILE

NOVI, MI 48376-0995

www.qualitychoice.com

MADE IN KOREA